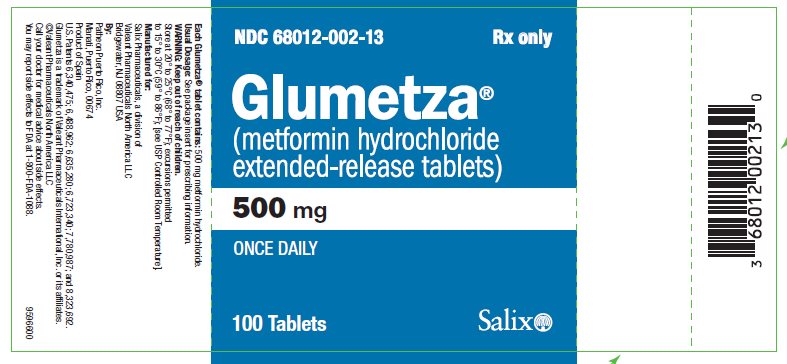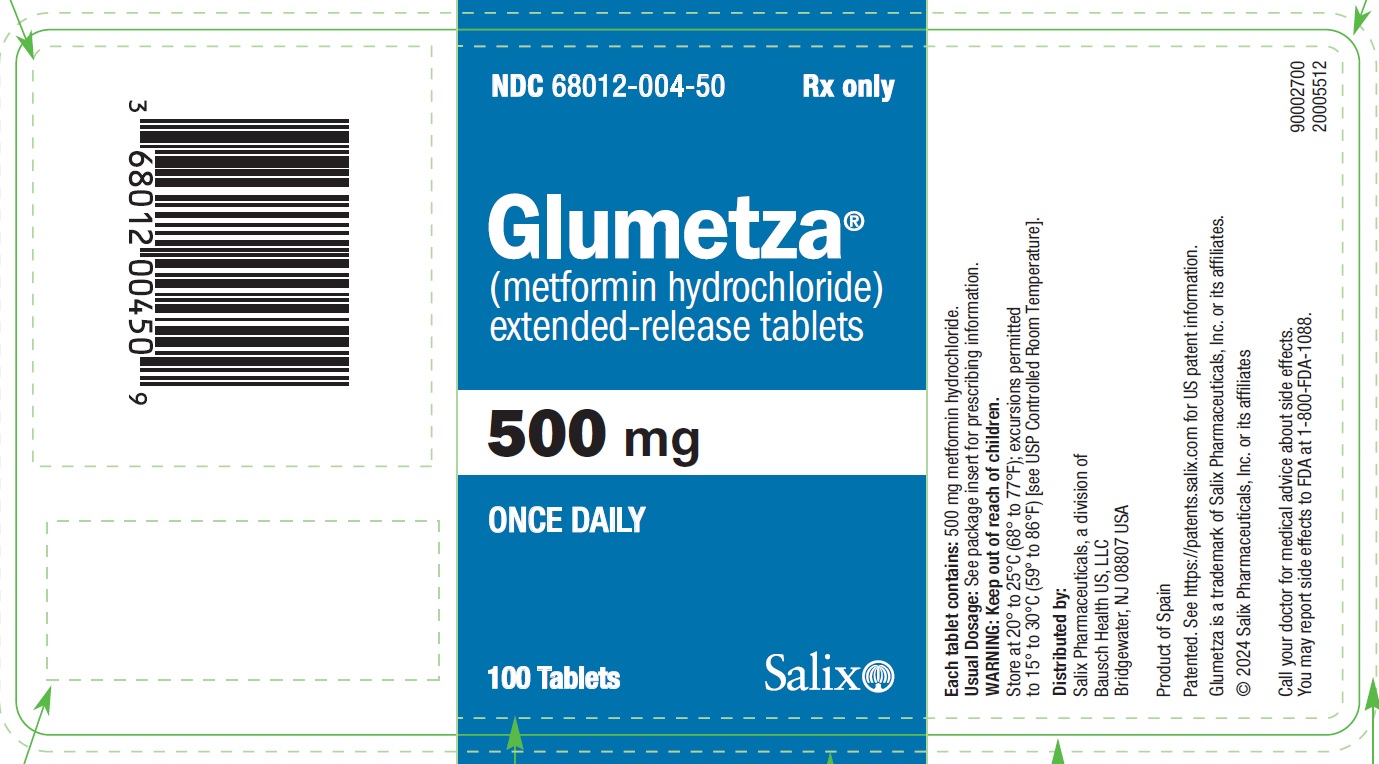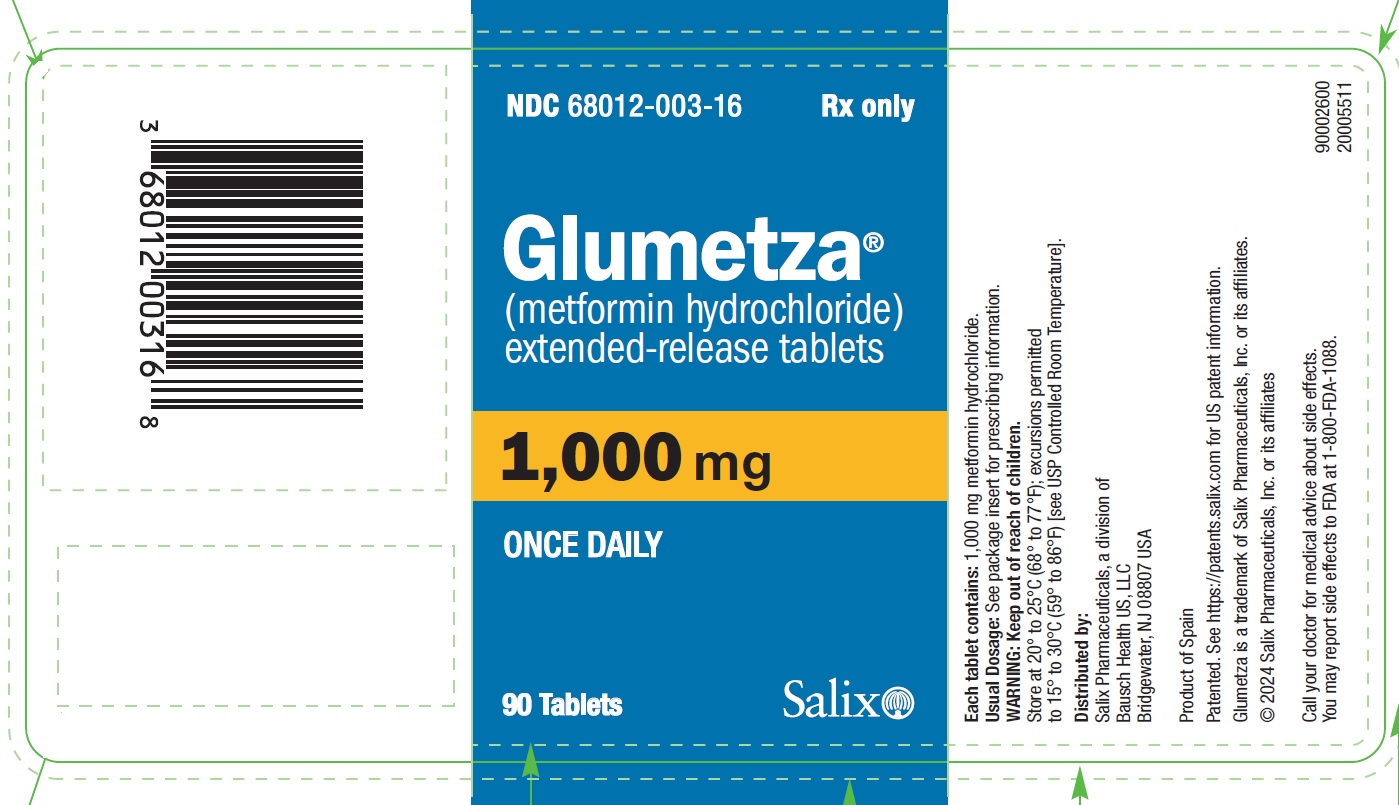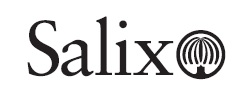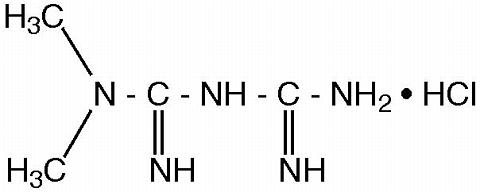 DRUG LABEL: Glumetza
NDC: 68012-002 | Form: TABLET, FILM COATED, EXTENDED RELEASE
Manufacturer: Santarus, Inc.
Category: prescription | Type: HUMAN PRESCRIPTION DRUG LABEL
Date: 20240227

ACTIVE INGREDIENTS: METFORMIN HYDROCHLORIDE 500 mg/1 1
INACTIVE INGREDIENTS: HYPROMELLOSE, UNSPECIFIED; MAGNESIUM STEARATE; MICROCRYSTALLINE CELLULOSE; POLYETHYLENE GLYCOL, UNSPECIFIED

HIGHLIGHTS OF PRESCRIBING INFORMATION

These highlights do not include all the information needed to use GLUMETZA safely and effectively. See full prescribing information for GLUMETZA.
GLUMETZA® (metformin hydrochloride) extended-release tablets, for oral use
Initial U.S. Approval: 1995

WARNING: LACTIC ACIDOSIS

See full prescribing information for complete boxed warning.

- Postmarketing cases of metformin-associated lactic acidosis have resulted in death, hypothermia, hypotension, and resistant bradyarrhythmias. Symptoms included malaise, myalgias, respiratory distress, somnolence, and abdominal pain. Laboratory abnormalities included elevated blood lactate levels, anion gap acidosis, increased lactate/pyruvate ratio; and metformin plasma levels generally >5 mcg/mL. (5.1)
- Risk factors include renal impairment, concomitant use of certain drugs, age ≥65 years old, radiological studies with contrast, surgery and other procedures, hypoxic states, excessive alcohol intake, and hepatic impairment. Steps to reduce the risk of and manage metformin-associated lactic acidosis in these high risk groups are provided in the Full Prescribing Information. (5.1)
- If lactic acidosis is suspected, discontinue GLUMETZA and institute general supportive measures in a hospital setting. Prompt hemodialysis is recommended. (5.1)

1 INDICATIONS AND USAGE

GLUMETZA is a biguanide indicated as an adjunct to diet and exercise to improve glycemic control in adults with type 2 diabetes mellitus. (1)

2 DOSAGE AND ADMINISTRATION

- Starting dose: 500 mg orally once daily with the evening meal (2.1)
- Increase the dose in increments of 500 mg every 1 to 2 weeks, up to a maximum of 2,000 mg once daily with the evening meal. (2.1)
- Patients receiving metformin hydrochloride (HCl) tablets may be switched to GLUMETZA once daily at the same total daily dose, up to 2,000 mg once daily. (2.1)
- Swallow GLUMETZA tablets whole and never crush, cut or chew. (2.1)

Renal Impairment:

- Prior to initiation, assess renal function with estimated glomerular filtration rate (eGFR). (2.2)
  - Do not use in patients with eGFR below 30 mL/minute/1.73 m^2.
  - Initiation is not recommended in patients with eGFR between 30 to 45 mL/minute/1.73 m^2.
  - Assess risk/benefit of continuing GLUMETZA if eGFR falls below 45 mL/minute/1.73 m^2.
  - Discontinue if eGFR falls below 30 mL/minute/1.73 m^2.

Discontinuation for Iodinated Contrast Imaging Procedures:

- GLUMETZA may need to be discontinued at time of, or prior to, iodinated contrast imaging procedures. (2.3)

3 DOSAGE FORMS AND STRENGTHS

GLUMETZA Extended-Release Tablets: 500 mg and 1,000 mg (3)

4 CONTRAINDICATIONS

- Severe renal impairment: (eGFR below 30 mL/minute/1.73 m^2) (4, 5.1)
- Known hypersensitivity to metformin (4)
- Acute or chronic metabolic acidosis, including diabetic ketoacidosis, with or without coma (4)

5 WARNINGS AND PRECAUTIONS

- Lactic Acidosis: See boxed warning. (5.1)
- Vitamin B12 Deficiency: Metformin may lower vitamin B12 levels. Monitor hematological parameters annually and vitamin B12 at 2 to 3 year intervals and manage any abnormalities. (5.2)
- Hypoglycemia with Concomitant Use with Insulin and Insulin Secretagogues: Increased risk of hypoglycemia when used in combination with insulin and/or an insulin secretagogue. Lower dose of insulin or insulin secretagogue may be required. (5.3)

6 ADVERSE REACTIONS

Adverse reactions occurring >5% in GLUMETZA clinical trials: hypoglycemia, diarrhea, and nausea. (6.1)

To report SUSPECTED ADVERSE REACTIONS, contact Salix Pharmaceuticals at 1-800-321-4576 or FDA at 1-800-FDA-1088 or www.fda.gov/medwatch.

7 DRUG INTERACTIONS

- Carbonic anhydrase inhibitors may increase risk of lactic acidosis. Consider more frequent monitoring. (7)
- Drugs that reduce metformin clearance (such as ranolazine, vandetanib, dolutegravir, and cimetidine) may increase the accumulation of metformin. Consider the benefits and risks of concomitant use. (7)
- Alcohol can potentiate the effect of metformin on lactate metabolism. Warn patients against excessive alcohol intake. (7)

8 USE IN SPECIFIC POPULATIONS

- Females and Males of Reproductive Potential: Advise premenopausal females of the potential for an unintended pregnancy. (8.3)
- Geriatric Use: Assess renal function more frequently. (8.5)
- Hepatic Impairment: Avoid use in patients with hepatic impairment. (8.7)

FULL PRESCRIBING INFORMATION

WARNING: LACTIC ACIDOSIS

Postmarketing cases of metformin-associated lactic acidosis have resulted in death, hypothermia, hypotension, and resistant bradyarrhythmias. The onset of metformin-associated lactic acidosis is often subtle, accompanied only by nonspecific symptoms such as malaise, myalgias, respiratory distress, somnolence, and abdominal pain. Metformin-associated lactic acidosis was characterized by elevated blood lactate levels (>5 mmol/Liter), anion gap acidosis (without evidence of ketonuria or ketonemia), an increased lactate/pyruvate ratio, and metformin plasma levels generally >5 mcg/mL [see Warnings and Precautions (5.1)].

Risk factors for metformin-associated lactic acidosis include renal impairment, concomitant use of certain drugs (e.g., carbonic anhydrase inhibitors such as topiramate), age 65 years old or greater, having a radiological study with contrast, surgery and other procedures, hypoxic states (e.g., acute congestive heart failure), excessive alcohol intake, and hepatic impairment.

Steps to reduce the risk of and manage metformin-associated lactic acidosis in these high risk groups are provided in the full prescribing information [see Dosage and Administration (2.2), Contraindications (4), Warnings and Precautions (5.1), and Drug Interactions (7)].

If metformin-associated lactic acidosis is suspected, immediately discontinue GLUMETZA and institute general supportive measures in a hospital setting. Prompt hemodialysis is recommended [see Warnings and Precautions (5.1)].

1 INDICATIONS AND USAGE

GLUMETZA is indicated as an adjunct to diet and exercise to improve glycemic control in adults with type 2 diabetes mellitus.

2 DOSAGE AND ADMINISTRATION

2.1 Adult Dosage and Administration

- The recommended starting dose of GLUMETZA is 500 mg orally once daily with the evening meal.
- Increase the dose in increments of 500 mg every 1 to 2 weeks on the basis of glycemic control and tolerability, up to a maximum of 2,000 mg once daily with the evening meal.
- Patients receiving metformin hydrochloride (HCl) may be switched to GLUMETZA once daily at the same total daily dose, up to 2,000 mg once daily.
- Swallow GLUMETZA whole and never crush, cut or chew.
- If a dose of GLUMETZA is missed, instruct patients not to take two doses the same day and to resume their usual dose of GLUMETZA with the next schedule dose.

2.2 Recommendations for Use in Renal Impairment

- Assess renal function prior to initiation of GLUMETZA and periodically thereafter.
- GLUMETZA is contraindicated in patients with an estimated glomerular filtration rate (eGFR) below 30 mL/minute/1.73 m^2.
- Initiation of GLUMETZA in patients with an eGFR between 30 to 45 mL/minute/1.73 m^2 is not recommended.
- In patients taking GLUMETZA whose eGFR later falls below 45 mL/minute/1.73 m^2, assess the benefit risk of continuing therapy.
- Discontinue GLUMETZA if the patient’s eGFR later falls below 30 mL/minute/1.73 m^2 [see Contraindications (4) and Warnings and Precautions (5.1)].

2.3 Discontinuation for Iodinated Contrast Imaging Procedures

Discontinue GLUMETZA at the time of, or prior to, an iodinated contrast imaging procedure in patients with an eGFR between 30 and 60 mL/minute/1.73 m^2; in patients with a history of liver disease, alcoholism or heart failure; or in patients who will be administered intra-arterial iodinated contrast. Re-evaluate eGFR 48 hours after the imaging procedure; restart GLUMETZA if renal function is stable [see Warnings and Precautions (5.1)].

3 DOSAGE FORMS AND STRENGTHS

GLUMETZA is available as:

• Extended-release tablets: 500 mg white, film-coated, oval-shaped tablets with “M500” on one side.

• Extended-release tablets: 1,000 mg white, film-coated, oval-shaped tablets with “M1000” on one side.

4 CONTRAINDICATIONS

GLUMETZA is contraindicated in patients with:

- Severe renal impairment (eGFR below 30 mL/minute/1.73 m^2) [see Warnings and Precautions (5.1)].
- Known hypersensitivity to metformin.
- Acute or chronic metabolic acidosis, including diabetic ketoacidosis, with or without coma.

5 WARNINGS AND PRECAUTIONS

5.1 Lactic Acidosis

There have been postmarketing cases of metformin-associated lactic acidosis, including fatal cases. These cases had a subtle onset and were accompanied by nonspecific symptoms such as malaise, myalgias, abdominal pain, respiratory distress, or increased somnolence; however, hypothermia, hypotension and resistant bradyarrhythmias have occurred with severe acidosis. Metformin-associated lactic acidosis was characterized by elevated blood lactate concentrations (>5 mmol/Liter), anion gap acidosis (without evidence of ketonuria or ketonemia), and an increased lactate/pyruvate ratio; metformin plasma levels were generally >5 mcg/mL. Metformin decreases liver uptake of lactate increasing lactate blood levels which may increase the risk of lactic acidosis, especially in patients at risk.

If metformin-associated lactic acidosis is suspected, general supportive measures should be instituted promptly in a hospital setting, along with immediate discontinuation of GLUMETZA. In GLUMETZA-treated patients with a diagnosis or strong suspicion of lactic acidosis, prompt hemodialysis is recommended to correct the acidosis and remove accumulated metformin (metformin HCl is dialyzable, with a clearance of up to 170 mL/minute under good hemodynamic conditions). Hemodialysis has often resulted in reversal of symptoms and recovery.

Educate patients and their families about the symptoms of lactic acidosis and if these symptoms occur, instruct them to discontinue GLUMETZA and report these symptoms to their healthcare provider.

For each of the known and possible risk factors for metformin-associated lactic acidosis, recommendations to reduce the risk of and manage metformin-associated lactic acidosis are provided below:

- Renal Impairment: The postmarketing metformin-associated lactic acidosis cases primarily occurred in patients with significant renal impairment. The risk of metformin accumulation and metformin-associated lactic acidosis increases with the severity of renal impairment because metformin is substantially excreted by the kidney. Clinical recommendations based upon the patient’s renal function include [see Dosage and Administration (2.2) and Clinical Pharmacology (12.3)]:
- Before initiating GLUMETZA, obtain an estimated glomerular filtration rate (eGFR).
- GLUMETZA is contraindicated in patients with an eGFR less than 30 mL/minute/1.73 m^2 [see Contraindications (4)].
- Initiation of GLUMETZA is not recommended in patients with eGFR between 30 to 45 mL/minute/1.73 m^2.
- Obtain an eGFR at least annually in all patients taking GLUMETZA. In patients at increased risk for the development of renal impairment (e.g., the elderly), renal function should be assessed more frequently.
- In patients taking GLUMETZA whose eGFR later falls below 45 mL/minute/1.73 m^2, assess the benefit and risk of continuing therapy.
- Drug Interactions: The concomitant use of GLUMETZA with specific drugs may increase the risk of metformin-associated lactic acidosis: those that impair renal function, result in significant hemodynamic change, interfere with acid-base balance or increase metformin accumulation [see Drug Interactions (7)]. Therefore, consider more frequent monitoring of patients.
- Age 65 or Greater: The risk of metformin-associated lactic acidosis increases with the patient’s age because elderly patients have a greater likelihood of having hepatic, renal, or cardiac impairment than younger patients. Assess renal function more frequently in elderly patients [see Use in Specific Populations (8.5)].
- Radiological Studies with Contrast: Administration of intravascular iodinated contrast agents in metformin-treated patients has led to an acute decrease in renal function and the occurrence of lactic acidosis. Stop GLUMETZA at the time of, or prior to, an iodinated contrast imaging procedure in patients with an eGFR between 30 and 60 mL/minute/1.73 m^2; in patients with a history of hepatic impairment, alcoholism, or heart failure; or in patients who will be administered intra-arterial iodinated contrast. Re-evaluate eGFR 48 hours after the imaging procedure, and restart GLUMETZA if renal function is stable.
- Surgery and Other Procedures: Withholding of food and fluids during surgical or other procedures may increase the risk for volume depletion, hypotension and renal impairment. GLUMETZA should be temporarily discontinued while patients have restricted food and fluid intake.
- Hypoxic States: Several of the postmarketing cases of metformin-associated lactic acidosis occurred in the setting of acute congestive heart failure (particularly when accompanied by hypoperfusion and hypoxemia). Cardiovascular collapse (shock), acute myocardial infarction, sepsis, and other conditions associated with hypoxemia have been associated with lactic acidosis and may also cause prerenal azotemia. When such events occur, discontinue GLUMETZA.
- Excessive Alcohol Intake: Alcohol potentiates the effect of metformin on lactate metabolism, and this may increase the risk of metformin-associated lactic acidosis. Warn patients against excessive alcohol intake while receiving GLUMETZA.
- Hepatic Impairment: Patients with hepatic impairment have developed cases of metformin-associated lactic acidosis. This may be due to impaired lactate clearance resulting in higher lactate blood levels. Therefore, avoid use of GLUMETZA in patients with clinical or laboratory evidence of hepatic disease.

5.2 Vitamin B12 Deficiency

In clinical trials of 29-week duration with metformin HCl tablets, a decrease to subnormal levels of previously normal serum vitamin B12 levels was observed in approximately 7% of patients. Such decrease, possibly due to interference with B12 absorption from the B12-intrinsic factor complex, may be associated with anemia but appears to be rapidly reversible with discontinuation of metformin or vitamin B12 supplementation. Certain individuals (those with inadequate vitamin B12 or calcium intake or absorption) appear to be predisposed to developing subnormal vitamin B12 levels. Measure hematologic parameters on an annual basis and vitamin B12 at 2 to 3 year intervals in patients on GLUMETZA and manage any abnormalities [see Adverse Reactions (6.1)].

5.3 Hypoglycemia with Concomitant Use with Insulin and Insulin Secretagogues

Insulin and insulin secretagogues (e.g., sulfonylurea) are known to cause hypoglycemia. GLUMETZA may increase the risk of hypoglycemia when combined with insulin and/or an insulin secretagogue. Therefore, a lower dose of insulin or insulin secretagogue may be required to minimize the risk of hypoglycemia when used in combination with GLUMETZA [see Drug Interactions (7)].

5.4 Macrovascular Outcomes

There have been no clinical studies establishing conclusive evidence of macrovascular risk reduction with GLUMETZA.

6 ADVERSE REACTIONS

6.1 Clinical Trials Experience

The following adverse reactions are discussed in more detail in other sections of the labeling:

- Lactic Acidosis [see Boxed Warning and Warnings and Precautions (5.1)]
- Vitamin B12 Deficiency [see Warnings and Precautions (5.2)]
- Hypoglycemia [see Warnings and Precautions (5.3)]

Because clinical trials are conducted under widely varying conditions, adverse reaction rates observed in the clinical trials of a drug cannot be directly compared to rates in the clinical trials of another drug and may not reflect the rates observed in practice. In clinical trials conducted in the U.S., over 1,000 patients with type 2 diabetes mellitus have been treated with GLUMETZA 1,500 to 2,000 mg/day in active-controlled and placebo-controlled studies with the 500 mg dosage form.

In the add-on to sulfonylurea study, patients receiving background glyburide therapy were randomized to receive add-on treatment of either one of three different regimens of GLUMETZA or placebo. In total, 431 patients received GLUMETZA and glyburide and 144 patients received placebo and glyburide. Adverse reactions reported in greater than 5% of patients treated with GLUMETZA that were more common in the combined GLUMETZA and glyburide group than in the placebo and glyburide group are shown in Table 1.

In 0.7% of patients treated with GLUMETZA and glyburide, diarrhea was responsible for discontinuation of study medication compared to no patients in the placebo and glyburide group.

Table 1: Adverse Reactions Reported by >5% [Adverse reactions that were more common in the GLUMETZA-treated than in the placebo-treated patients.] of Patients for the Combined GLUMETZA Groups Versus Placebo Group
Adverse Reaction | GLUMETZA + Glyburide (n=431) | Placebo + Glyburide (n=144)
Hypoglycemia | 14% | 5%
Diarrhea | 13% | 6%
Nausea | 7% | 4%

Laboratory Tests
Vitamin B12 Concentrations

In clinical trials of 29-week duration with metformin HCl tablets, a decrease to subnormal levels of previously normal serum vitamin B12 levels was observed in approximately 7% of patients.

6.2 Postmarketing Experience

The following adverse reactions have been identified during post-approval use of GLUMETZA. Because these reactions are reported voluntarily from a population of uncertain size, it is not always possible to reliably estimate their frequency or establish a causal relationship to drug exposure.

Cholestatic, hepatocellular, and mixed hepatocellular liver injury have been reported with postmarketing use of metformin.

7 DRUG INTERACTIONS

Table 2 presents clinically significant drug interactions with GLUMETZA.

Table 2: Clinically Significant Drug Interactions with GLUMETZA
Carbonic Anhydrase Inhibitors
Clinical Impact: | Carbonic anhydrase inhibitors frequently cause a decrease in serum bicarbonate and induce non-anion gap, hyperchloremic metabolic acidosis. Concomitant use of these drugs with GLUMETZA may increase the risk for lactic acidosis.
Intervention: | Consider more frequent monitoring of these patients.
Examples: | Topiramate, zonisamide, acetazolamide or dichlorphenamide.
Drugs that Reduce GLUMETZA Clearance
Clinical Impact: | Concomitant use of drugs that interfere with common renal tubular transport systems involved in the renal elimination of metformin (e.g., organic cationic transporter-2 [OCT2] / multidrug and toxin extrusion [MATE] inhibitors) could increase systemic exposure to metformin and may increase the risk for lactic acidosis [see Clinical Pharmacology (12.3)].
Intervention: | Consider the benefits and risks of concomitant use with GLUMETZA.
Examples: | Ranolazine, vandetanib, dolutegravir, and cimetidine.
Alcohol
Clinical Impact: | Alcohol is known to potentiate the effect of metformin on lactate metabolism.
Intervention: | Warn patients against excessive alcohol intake while receiving GLUMETZA.
Insulin Secretagogues or Insulin
Clinical Impact: | Coadministration of GLUMETZA with an insulin secretagogue (e.g., sulfonylurea) or insulin may increase the risk of hypoglycemia.
Intervention: | Patients receiving an insulin secretagogue or insulin may require lower doses of; the insulin secretagogue or insulin.
Drugs Affecting Glycemic Control
Clinical Impact: | Certain drugs tend to produce hyperglycemia and may lead to loss of glycemic control.
Intervention: | When such drugs are administered to a patient receiving GLUMETZA, observe the patient closely for loss of blood glucose control. When such drugs are withdrawn from a patient receiving GLUMETZA, observe the patient closely for hypoglycemia.
Examples: | Thiazides and other diuretics, corticosteroids, phenothiazines, thyroid products, estrogens, oral contraceptives, phenytoin, nicotinic acid, sympathomimetics, calcium channel blockers, and isoniazid.

8 USE IN SPECIFIC POPULATIONS

8.1 Pregnancy

Risk Summary

Limited data with GLUMETZA in pregnant women are not sufficient to determine a drug-associated risk for major birth defects or miscarriage. Published studies with metformin use during pregnancy have not reported a clear association with metformin and major birth defect or miscarriage risk [see Data]. There are risks to the mother and fetus associated with poorly controlled diabetes mellitus in pregnancy [see Clinical Considerations].

No adverse developmental effects were observed when metformin was administered to pregnant Sprague Dawley rats and rabbits during the period of organogenesis at doses up to 3 and 1 times, respectively, a 2,000 mg clinical dose, based on body surface area [see Data].

The estimated background risk of major birth defects is 6–10% in women with pregestational diabetes mellitus with an HbA1c >7 and has been reported to be as high as 20–25% in women with an HbA1c >10. The estimated background risk of miscarriage for the indicated population is unknown. In the U.S. general population, the estimated background risk of major birth defects and miscarriage in clinically recognized pregnancies is 2–4% and 15–20%, respectively.

Clinical Considerations

Disease-associated maternal and/or embryo/fetal risk
Poorly controlled diabetes mellitus in pregnancy increases the maternal risk for diabetic ketoacidosis, pre-eclampsia, spontaneous abortions, preterm delivery, stillbirth and delivery complications. Poorly controlled diabetes mellitus increases the fetal risk for major birth defects, stillbirth, and macrosomia-related morbidity.

Data

Human Data
Published data from postmarketing studies have not reported a clear association with metformin and major birth defects, miscarriage, or adverse maternal or fetal outcomes when metformin was used during pregnancy. However, these studies cannot definitely establish the absence of any metformin-associated risk because of methodological limitations, including small sample size and inconsistent comparator groups.

Animal Data
Metformin HCl was not teratogenic or embyrolethal when administered to rats prior to pregnancy through the period of organogenesis at doses up to 900 mg/kg, or when administered to rabbits during the period of organogenesis at doses up to 90 mg/kg.

8.2 Lactation

Risk Summary

Limited published studies report that metformin is present in human milk [see Data]. However, there is insufficient information to determine the effects of metformin on the breastfed infant and no available information on the effects of metformin on milk production. Therefore, the developmental and health benefits of breastfeeding should be considered along with the mother’s clinical need for GLUMETZA and any potential adverse effects on the breastfed child from GLUMETZA or from the underlying maternal condition.

Data

Published clinical lactation studies report that metformin is present in human milk which resulted in infant doses approximately 0.11% to 1% of the maternal weight-adjusted dosage and a milk/plasma ratio ranging between 0.13 and 1. However, the studies were not designed to definitely establish the risk of use of metformin during lactation because of small sample size and limited adverse event data collected in infants.

8.3 Females and Males of Reproductive Potential

Discuss the potential for unintended pregnancy with premenopausal women as therapy with GLUMETZA may result in ovulation in some anovulatory women.

8.4 Pediatric Use

Safety and effectiveness of GLUMETZA in pediatric patients have not been established.

8.5 Geriatric Use

Clinical studies of GLUMETZA did not include sufficient numbers of subjects aged 65 and over to determine whether they respond differently from younger subjects. In general, dose selection for an elderly patient should be cautious, usually starting at the low end of the dosing range, reflecting the greater frequency of decreased hepatic, renal, or cardiac function, and of concomitant disease or other drug therapy and the higher risk of lactic acidosis. Assess renal function more frequently in elderly patients [see Dosage and Administration (2.2) and Warnings and Precautions (5.1)].

8.6 Renal Impairment

Metformin is substantially excreted by the kidney, and the risk of metformin accumulation and lactic acidosis increases with the degree of renal impairment. GLUMETZA is contraindicated in severe renal impairment, patients with an estimated glomerular filtration rate (eGFR) below 30 mL/minute/1.73 m^2 [see Dosage and Administration (2.2), Contraindications (4), Warnings and Precautions (5.1), and Clinical Pharmacology (12.3)].

8.7 Hepatic Impairment

Use of metformin in patients with hepatic impairment has been associated with some cases of lactic acidosis.

GLUMETZA is not recommended in patients with hepatic impairment [see Warnings and Precautions (5.1)].

10 OVERDOSAGE

Overdose of metformin HCl has occurred, including ingestion of amounts greater than 50 grams. Hypoglycemia was reported in approximately 10% of cases, but no causal association with metformin has been established. Lactic acidosis has been reported in approximately 32% of metformin overdose cases [see Warnings and Precautions (5.1)]. Metformin is dialyzable with a clearance of up to 170 mL/minute under good hemodynamic conditions. Therefore, hemodialysis may be useful for removal of accumulated drug from patients in whom metformin overdosage is suspected.

11 DESCRIPTION

GLUMETZA contains the biguanide antihyperglycemic agent metformin in the form of monohydrochloride salt. The chemical name of metformin hydrochloride is N,N-dimethylimidodicarbonimidic diamide hydrochloride. The structural formula is as shown:

Metformin hydrochloride is a white to off-white crystalline compound with a molecular formula of C4H11N5•HCl and a molecular weight of 165.63. Metformin hydrochloride is freely soluble in water and is practically insoluble in acetone, ether, and chloroform. The pKa of metformin is 12.4. The pH of a 1% aqueous solution of metformin hydrochloride is 6.68.

GLUMETZA tablets contain 500 mg or 1,000 mg of metformin hydrochloride, which is equivalent to 389.93 mg or 779.86 mg metformin, respectively. Each 500 mg tablet contains coloring, hypromellose, magnesium stearate, microcrystalline cellulose and polyethylene oxide. Each 1,000 mg tablet contains colloidal silicon dioxide, polyvinyl alcohol, crospovidone, glyceryl dibehenate, polyacrylate dispersion, hypromellose, talc, polyethylene glycol, titanium dioxide, simethicone emulsion, polysorbate and coloring.

12 CLINICAL PHARMACOLOGY

12.1 Mechanism of Action

Metformin is a biguanide that improves glucose tolerance in patients with type 2 diabetes, lowering both basal and postprandial plasma glucose. Metformin decreases hepatic glucose production, decreases intestinal absorption of glucose, and improves insulin sensitivity by increasing peripheral glucose uptake and utilization. With metformin therapy, insulin secretion remains unchanged while fasting insulin levels and day-long plasma insulin response may decrease.

12.3 Pharmacokinetics

Absorption

Following a single oral dose of 1,000 mg (2x500 mg tablets) GLUMETZA after a meal, the time to reach maximum plasma metformin concentration (Tmax) is achieved at approximately 7-8 hours. In both single- and multiple-dose studies in healthy subjects, once daily 1,000 mg (2x500 mg tablets) dosing provides equivalent systemic exposure, as measured by area under the curve (AUC), and up to 35% higher Cmax, of metformin relative to the immediate-release given as 500 mg twice daily. At usual clinical doses and dosing schedules of metformin, steady state plasma concentrations of metformin are reached within 24-48 hours and are generally <1 mcg/mL.

Single oral doses of GLUMETZA from 500 mg to 2,500 mg resulted in less than proportional increase in both AUC and Cmax.

Effect of food: Low-fat and high-fat meals increased the systemic exposure (as measured by AUC) from GLUMETZA tablets by about 38% and 73%, respectively, relative to fasting. Both meals prolonged metformin Tmax by approximately 3 hours but Cmax was not affected.

In a two-way, single-dose, crossover study in healthy volunteers, the 1,000 mg tablet was found to be similar to two 500 mg tablets under fed conditions based on equivalent Cmax and AUCs for the two formulations.

Distribution

The apparent volume of distribution (V/F) of metformin following single oral doses of 850 mg metformin HCl averaged 654±358 L. Metformin is negligibly bound to plasma proteins. Metformin partitions into erythrocytes, most likely as a function of time.

Metabolism

Intravenous, single-dose studies in healthy subjects demonstrate that metformin is excreted unchanged in the urine and does not undergo hepatic metabolism (no metabolites have been identified in humans), nor biliary excretion.

Excretion

Renal clearance is approximately 3.5 times greater than creatinine clearance, which indicates that tubular secretion is the major route of metformin elimination. Following oral administration, approximately 90% of the absorbed drug is eliminated via the renal route within the first 24 hours, with a plasma elimination half-life of approximately 6.2 hours. In blood, the elimination half-life is approximately 17.6 hours, suggesting that the erythrocyte mass may be a compartment of distribution.

Special Populations

Renal Impairment

Following a single-dose administration of GLUMETZA 500 mg in subjects with mild and moderate renal impairment, the oral and renal clearance of metformin were decreased by 33% and 50% and 16% and 53%, respectively. Metformin peak and systemic exposure was 27% and 61% greater, respectively in subjects with mild renal impairment and 74% and 2.36-fold greater in subjects with moderate renal impairment as compared to healthy subjects [see Dosage and Administration (2.2), Contraindications (4), and Warnings and Precautions (5.1)].

Hepatic Impairment

No pharmacokinetic studies of GLUMETZA have been conducted in subjects with hepatic impairment [see Warnings and Precautions (5.1) and Use in Specific Populations (8.7)].

Geriatrics

Limited data from controlled pharmacokinetic studies of metformin HCl in healthy elderly subjects suggest that total plasma clearance of metformin is decreased by 35%, the half-life is prolonged by 64% and Cmax is increased by 76%, compared to healthy young subjects. From these data, it appears that the change in metformin pharmacokinetics with aging is primarily accounted for by a change in renal function [see Dosage and Administration (2) and Warnings and Precautions (5.1)].

Gender

In the pharmacokinetic studies in healthy volunteers, there were no important differences between male and female subjects with respect to metformin AUC and t1/2. However, Cmax for metformin was 40% higher in female subjects as compared to males. In controlled clinical studies in patients with type 2 diabetes, the antihyperglycemic effect of metformin HCl tablets was comparable in males and females. The gender differences for Cmax are unlikely to be clinically important.

Race

A trend towards 10% higher metformin Cmax and AUC values for metformin are obtained in Asian subjects when compared to Caucasian, Hispanic and Black subjects. The differences between the Asian and Caucasian groups are unlikely to be clinically important. In controlled clinical studies of metformin HCl in patients with type 2 diabetes, the antihyperglycemic effect was comparable in whites (n=249), blacks (n=51) and Hispanics (n=24).

Pediatrics

There are no available pharmacokinetic data with GLUMETZA in pediatric patients.

Drug Interactions

Specific pharmacokinetic drug interaction studies with GLUMETZA have not been performed except for one with glyburide. However, such studies have been performed on metformin HCl tablets.

Table 3: Effect of Coadministered Drug on Plasma Metformin Systemic Exposure
Coadministered Drug | Dose of Coadministered Drug [All metformin HCl and coadministered drugs were given as single doses.] | Dose of Metformin HCl | Geometric Mean Ratio (ratio with/ without coadministered drug); No Effect=1.00
Coadministered Drug | Dose of Coadministered Drug [All metformin HCl and coadministered drugs were given as single doses.] | Dose of Metformin HCl | AUC [AUC=AUC0-inf] | Cmax
No dosing adjustments required for the following:
Glyburide | 5 mg | 500 mg [GLUMETZA (metformin hydrochloride) extended-release tablets 500 mg] | 0.98 [Ratio of arithmetic means] | 0.99
Furosemide | 40 mg | 850 mg | 1.09 | 1.22
Nifedipine | 10 mg | 850 mg | 1.16 | 1.21
Propranolol | 40 mg | 850 mg | 0.90 | 0.94
Ibuprofen | 400 mg | 850 mg | 1.05 | 1.07
Cationic drugs that are eliminated by renal tubular secretion may increase the accumulation of metformin: [see Warnings and Precautions (5.1) and Drug Interactions (7)].
Cimetidine | 400 mg | 850 mg | 1.40 | 1.61
Carbonic anhydrase inhibitors may cause metabolic acidosis: [see Warnings and Precautions (5.1) and Drug Interactions (7)].
Topiramate | 100 mg [At steady state with topiramate 100 mg every 12 hours and metformin 500 mg every 12 hours; AUC=AUC0-12h] | 500 mg | 1.25 | 1.17

Table 4: Effect of Metformin on Coadministered Drug Systemic Exposure
Coadministered Drug | Dose of Coadministered Drug [All metformin HCl and coadministered drugs were given as single doses.] | Dose of Metformin HCl | Geometric Mean Ratio (ratio with/ without coadministered drug); No effect=1.00
Coadministered Drug | Dose of Coadministered Drug [All metformin HCl and coadministered drugs were given as single doses.] | Dose of Metformin HCl | AUC [AUC=AUC0-inf unless otherwise noted] | Cmax
No dosing adjustments required for the following:
Glyburide | 5 mg | 500 mg [AUC0-24 hr reported] | 0.78 [Ratio of arithmetic means, p-value of difference <0.05] | 0.63
Furosemide | 40 mg | 850 mg | 0.87 | 0.69
Nifedipine | 10 mg | 850 mg | 1.10 | 1.08
Propranolol | 40 mg | 850 mg | 1.01 | 0.94
Ibuprofen | 400 mg | 850 mg | 0.97 [Ratio of arithmetic means] | 1.01
Cimetidine | 400 mg | 850 mg | 0.95 | 1.01

13 NONCLINICAL TOXICOLOGY

13.1 Carcinogenesis, Mutagenesis, Impairment of Fertility

Long-term carcinogenicity studies have been performed in Sprague Dawley rats at doses of 150, 300, and 450 mg/kg/day in males and 150, 450, 900, and 1,200 mg/kg/day in females. These doses are approximately 2, 4, and 8 times in males, and 3, 7, 12, and 16 times in females of the maximum recommended human daily dose of 2,000 mg based on body surface area comparisons. No evidence of carcinogenicity with metformin was found in either male or female rats. A carcinogenicity study was also performed in Tg.AC transgenic mice at doses up to 2,000 mg applied dermally. No evidence of carcinogenicity was observed in male or female mice.

Genotoxicity assessments in the Ames test, gene mutation test (mouse lymphoma cells), chromosomal aberrations test (human lymphocytes) and in vivo mouse micronucleus tests were negative. Fertility of male or female rats was not affected by metformin when administered at doses up to 600 mg/kg/day, which is approximately 3 times the maximum recommended human daily dose based on body surface area comparisons.

14 CLINICAL STUDIES

In a multicenter, randomized, double-blind, active-controlled, dose-ranging, parallel group study conducted in patients type 2 diabetes mellitus, GLUMETZA 1,500 mg once daily, GLUMETZA 1,500 per day in divided doses (500 mg in the morning and 1,000 mg in the evening), and GLUMETZA 2,000 mg once daily were compared to immediate-release metformin HCl tablets 1,500 mg per day in divided doses (500 mg in the morning and 1,000 mg in the evening). This study included patients (n=338) who were newly diagnosed with diabetes, patients treated only with diet and exercise, patients treated with a single antidiabetic medication (sulfonylureas, alpha-glucosidase inhibitors, thiazolidinediones, or meglitinides), and patients (n=368) receiving metformin HCl tablets up to 1,500 mg/day plus a sulfonylurea at a dose equal to or less than one-half the maximum dose. Patients who were enrolled on monotherapy or combination antidiabetic therapy underwent a 6-week washout. Patients randomized to GLUMETZA began titration from 1,000 mg/day up to their assigned treatment dose over 3 weeks. Patients randomized to immediate-release metformin initiated 500 mg twice daily for 1 week followed by 500 mg with breakfast and 1,000 mg with dinner for the second week. The 3-week treatment period was followed by an additional 21-week period at the randomized dose. The results are presented in Table 5.

Table 5: Mean Changes from Baseline in HbA1c and Fasting Plasma Glucose at Week 24 Comparing GLUMETZA versus Metformin HCl Tablets [Immediate-release metformin HCl tablets] in Patients with Type 2 Diabetes Mellitus
 | GLUMETZA |  |  | Metformin HCl Tablets 1,500 mg in Divided Doses (n=174)
 | 1,500 mg Once Daily (n=178) | 1,500 mg in Divided Doses (n=182) | 2,000 mg Once Daily (n=172) | Metformin HCl Tablets 1,500 mg in Divided Doses (n=174)
HbA1c (%), N | 169 | 175 | 159 | 170
Baseline | 8.2 | 8.5 | 8.3 | 8.7
Mean Change at Final Visit | -0.7 | -0.7 | -1.1 | -0.7
Mean Difference from Metformin HCl Tablets (98.4% CI) | 0 (-0.3, 0.3) | 0 (-0.3, 0.3) | -0.4 (-0.7, -0.1) | N/A
Fasting Plasma Glucose (mg/dL), N | 175 | 179 | 170 | 172
Baseline | 190 | 192.3 | 184 | 197
Mean Change at Final Visit | -39 | -32 | -42 | -32
Mean Difference from Metformin HCl Tablets (95% CI) | -6 (-15, 2) | 0 (-8, 9) | -10 (-19, -1) | N/A

Mean baseline body weight was 88.2 kg, 90.5 kg, 87.7 kg and 88.7 kg in the GLUMETZA 1,500 mg once daily, GLUMETZA 1,500 mg in divided doses, GLUMETZA 2,000 mg once daily and metformin HCl tablets 1,500 mg in divided doses arms, respectively. Mean change in body weight from baseline to week 24 was -0.9 kg, -0.7 kg, -1.1 kg, and -0.9 kg in the GLUMETZA 1,500 mg once daily, GLUMETZA 1,500 mg in divided doses, GLUMETZA 2,000 mg once daily and metformin HCl tablets 1,500 mg in divided doses arms, respectively.

A double-blind, randomized, placebo-controlled (glyburide add-on) multicenter study enrolled patients with type 2 diabetes mellitus who were newly diagnosed or treated with diet and exercise (n=144), or who were receiving monotherapy with metformin, sulfonylureas, alpha-glucosidase inhibitors, thiazolidinediones, or meglitinides, or treated with combination therapy consisting of metformin HCl/glyburide at doses up to 1,000 mg metformin + 10 mg glyburide per day (or equivalent doses of glipizide or glimepiride up to half the maximum therapeutic dose) (n=431). All patients were stabilized on glyburide for a 6-week run-in period, and then randomized to 1 of 4 treatments: placebo + glyburide (glyburide alone); GLUMETZA 1,500 mg once a day + glyburide, GLUMETZA 2,000 mg once a day + glyburide, or GLUMETZA 1,000 mg twice a day + glyburide. A 3-week GLUMETZA titration period was followed by a 21-week maintenance treatment period. Use of insulin and oral hypoglycemic agents other than the study drugs were prohibited. The results are presented in Table 6.

Table 6: Mean Changes from Baseline in HbA1c and Fasting Plasma Glucose at Week 24 for the GLUMETZA + Glyburide Groups and Placebo+ Glyburide Treatment Group in Patients with Type 2 Diabetes Mellitus
 | GLUMETZA + Glyburide [Glyburide was administered as 10 mg at breakfast and 5 mg at dinner.] |  |  | Placebo + Glyburide (n=144)
 | 1,500 mg Once Daily (n=144) | 1,000 mg Twice Daily (n=141) | 2,000 mg Once Daily (n=146) | Placebo + Glyburide (n=144)
HbA1c (%), N | 136 | 136 | 144 | 141
Baseline | 7.9 | 7.8 | 7.7 | 8.1
Mean Change at Final Visit | -0.7 | -0.8 | -0.7 | -0.1
Mean Difference from Glyburide Alone (95% CI) | -0.8 [p-value for pairwise comparison <0.001] (-1.0, -0.6) | -0.9 (-1.1, -0.7) | -0.8 (-1.0, -0.6) | N/A
Fasting Plasma Glucose (mg/dL), N | 143 | 141 | 145 | 144
Baseline | 163 | 163 | 159 | 164
Mean Change at Final Visit | -14 | -16 | -9 | 16
Mean Difference from Glyburide Alone (95% CI) | -29.2 (-39, -20) | -31.2 (-41, -22) | -24.9 (-35, -15) | N/A

Mean baseline body weight was 89.4 kg, 103.7 kg, 102.9 kg and 95.6 kg in the GLUMETZA 1,500 mg once daily, GLUMETZA 1,500 mg in divided doses, GLUMETZA 2,000 mg once daily and metformin HCl tablets 1,500 mg in divided doses arms, respectively. Mean change in body weight from baseline to week 24 was 0.3 kg, 0.1 kg, 0 kg, and 0.7 kg in the GLUMETZA 1,500 mg once daily, GLUMETZA 1,500 mg in divided doses, GLUMETZA 2,000 mg once daily and metformin HCl tablets 1,500 mg in divided doses arms, respectively.

16 HOW SUPPLIED/STORAGE AND HANDLING

GLUMETZA is supplied as:

500 mg | Bottles of 100 | NDC 68012-004-50 | white, film-coated, oval-shaped, extended-release; tablets with “M500” on one side.
1,000 mg | Bottles of 90 | NDC 68012-003-16 | white, film-coated, oval-shaped, extended-release; tablets with “M1000” on one side.

Store at 20° to 25°C (68° to 77°F); excursions permitted to 15° to 30°C (59° to 86°F) [see USP Controlled Room Temperature].

17 PATIENT COUNSELING INFORMATION

Advise the patient to read the FDA-approved patient labeling (Patient Information).

Lactic Acidosis:

Explain the risks of lactic acidosis, its symptoms, and conditions that predispose to its development. Advise patients to discontinue GLUMETZA immediately and to promptly notify their healthcare provider if unexplained hyperventilation, myalgias, malaise, unusual somnolence or other nonspecific symptoms occur. Counsel patients against excessive alcohol intake and inform patients about importance of regular testing of renal function while receiving GLUMETZA. Instruct patients to inform their doctor that they are taking GLUMETZA prior to any surgical or radiological procedure, as temporary discontinuation may be required [see Warnings and Precautions (5.1)].

Hypoglycemia:
Inform patients that hypoglycemia may occur when GLUMETZA is coadministered with oral sulfonylureas and insulin. Explain to patients receiving concomitant therapy the risks of hypoglycemia, its symptoms and treatment, and conditions that predispose to its development [see Warnings and Precautions (5.3)].

Vitamin B12 Deficiency:

Inform patients about importance of regular hematological parameters while receiving GLUMETZA [see Warnings and Precautions (5.2)].

Females of Reproductive Age:

Inform females that treatment with GLUMETZA may result in ovulation in some premenopausal anovulatory women which may lead to unintended pregnancy [see Use in Specific Populations (8.3)].

Administration Information:

Inform patients that GLUMETZA must be swallowed whole and not crushed, cut, or chewed, and that the inactive ingredients may occasionally be eliminated in the feces as a soft mass that may resemble the original tablet.

Distributed by:
Salix Pharmaceuticals, a division of
Bausch Health US, LLC
Bridgewater, NJ 08807 USA

Manufactured by:
Bausch Health Companies Inc.
Steinbach, MB R5G 1Z7, Canada

Patented. See https://patents.salix.com for US patent information.
Glumetza is a trademark of Salix Pharmaceuticals, Inc. or its affiliates.
© 2024 Salix Pharmaceuticals, Inc. or its affiliates 9618905 20005381

PATIENT INFORMATION

GLUMETZA® (Gloo-met-za)

(metformin hydrochloride)

extended-release tablets, for oral use

What is the most important information I should know about GLUMETZA?

GLUMETZA can cause serious side effects, including:

Lactic acidosis. Metformin hydrochloride, the medicine in GLUMETZA, can cause a rare, but serious side effect called lactic acidosis (a buildup of lactic acid in the blood) that can cause death. Lactic acidosis is a medical emergency and must be treated in the hospital.

Stop taking GLUMETZA and call your doctor right away if you get any of the following symptoms of lactic acidosis:

- feel very weak and tired
- have unusual (not normal) muscle pain
- have trouble breathing
- have unexplained stomach or intestinal problems with nausea and vomiting, or diarrhea

• have unusual sleepiness or sleep longer than usual

• feel cold, especially in your arms and legs

• feel dizzy or lightheaded

• have a slow or irregular heartbeat

You have a higher chance of getting lactic acidosis if you:

- have severe kidney problems. See “Do not take GLUMETZA if you”
- have liver problems.
- drink a lot of alcohol (very often or short-term “binge” drinking).
- get dehydrated (lose a large amount of body fluids). This can happen if you are sick with a fever, vomiting, or diarrhea. Dehydration can also happen when you sweat a lot with activity or exercise and do not drink enough fluids.
- have certain x-ray tests with injectable dyes or contrast agents.
- have surgery or other procedure for which you need to restrict the amount of food and liquid you eat and drink.
- have congestive heart failure.
- have a heart attack, severe infection, or stroke.
- are 65 years of age or older.

Tell your doctor if you have any of the problems in the list above.

Tell your doctor that you are taking GLUMETZA before you have surgery or x-ray tests. Your doctor may need to stop GLUMETZA for a while if you have surgery or certain x-ray tests.

GLUMETZA can have other serious side effects. See “What are the possible side effects of GLUMETZA?”.

What is GLUMETZA?

- GLUMETZA is a prescription medicine that contains metformin hydrochloride. GLUMETZA is used with diet and exercise to help control high blood sugar (hyperglycemia) in adults with type 2 diabetes.
It is not known if GLUMETZA is safe and effective in children.

Do not take GLUMETZA if you:

- have severe kidney problems.
- are allergic to metformin hydrochloride or any of the ingredients in GLUMETZA. See the end of this Patient Information leaflet for a complete list of ingredients in GLUMETZA.
- have a condition called metabolic acidosis, including diabetic ketoacidosis (high levels of certain acids called “ketones” in your blood or urine).

Before taking GLUMETZA tell your doctor about all of your medical conditions, including if you:

- have a history or risk for diabetic ketoacidosis. See “Do not take GLUMETZA if you:”.
- have kidney problems.
- have liver problems.
- have heart problems, including congestive heart failure.
- are 65 years of age or older.
- drink alcohol very often, or drink a lot of alcohol in short-term “binge” drinking.
- are taking insulin or a sulfonylurea medicine.
- are pregnant or plan to become pregnant. It is not known if GLUMETZA can harm your unborn baby. If you are pregnant, talk with your doctor about the best way to control your blood sugar while you are pregnant.
- are a woman who has not gone through menopause (premenopausal) who does not have periods regularly or at all. GLUMETZA can cause the release of an egg from an ovary in a woman (ovulation). This can increase your chance of getting pregnant.
- are breastfeeding or plan to breastfeed. GLUMETZA can pass into your breast milk. Talk with your doctor about the best way to feed your baby while you take GLUMETZA.

Tell your doctor about all the medicines you take, including prescription and over-the-counter medicines, vitamins and herbal supplements. Know the medicines you take. Keep a list of them to show your doctor and pharmacist. Talk to your doctor before you start any new medicine.

GLUMETZA may affect the way other medicines work, and other medicines may affect how GLUMETZA works.

How should I take GLUMETZA?

- Take GLUMETZA exactly as your doctor tells you.
- GLUMETZA should be taken 1 time each day with your evening meal to help decrease an upset stomach.
- Swallow GLUMETZA tablets whole. Do not crush, cut, or chew the tablets.
- You may sometimes pass a soft mass in your stools (bowel movement) that looks like GLUMETZA tablets. This is normal and will not affect the way GLUMETZA works.
- When your body is under some type of stress, such as fever, trauma (such as a car accident), infection, or surgery, the amount of diabetes medicine that you need may change. Tell your doctor right away if you have any of these problems.
- Your doctor should do blood tests to check how well your kidneys are working before and during your treatment with GLUMETZA.
- Your doctor will check your diabetes with regular blood tests, including your blood sugar levels and your hemoglobin A1C.
- Low blood sugar (hypoglycemia) can happen more often when GLUMETZA is taken with certain other diabetes medicines. Talk to your doctor about how to prevent, recognize, and manage low blood sugar. See “What are the possible side effects of GLUMETZA?”.
- Check your blood sugar as your doctor tells you to.
- Stay on your prescribed diet and exercise program while taking GLUMETZA.
- If you miss a dose of GLUMETZA, take your next dose at the normal schedule. Do not take 2 doses of GLUMETZA on the same day.
- If you take too much GLUMETZA, call your doctor or go to the nearest hospital emergency room right away.

What should I avoid while taking GLUMETZA?

Do not drink a lot of alcoholic drinks while taking GLUMETZA. This means you should not binge drink for short periods, and you should not drink a lot of alcohol on a regular basis. Alcohol can increase the chance of getting lactic acidosis.

What are the possible side effects of GLUMETZA?

GLUMETZA can cause serious side effects, including:

- See “What is the most important information I should know about GLUMETZA?”.
- Low vitamin B12 (vitamin B12 deficiency). Using GLUMETZA may cause a decrease in the amount of vitamin B12 in your blood, especially if you have had low vitamin B12 levels before. Your doctor may do blood tests to check your vitamin B12 levels.
- Low blood sugar (hypoglycemia). Low blood sugar is a serious, but common, side effect of GLUMETZA. If you take GLUMETZA with another medicine that can cause low blood sugar, such as sulfonylureas or insulin, you have a higher risk of getting low blood sugar. The dose of your sulfonylurea medicine or insulin may need to be lowered while you take GLUMETZA. Signs and symptoms of low blood sugar may include:
- headache
- drowsiness
- weakness
- irritability
- hunger
- fast heartbeat
- confusion
- shaking or feeling jittery
- dizziness
- sweating

The most common side effects of GLUMETZA include:

- diarrhea
- nausea

These are not all of the possible side effects of GLUMETZA.

Call your doctor for medical advice about side effects. You may report side effects to FDA at 1-800-FDA-1088.

How should I store GLUMETZA?

- Store GLUMETZA at room temperature between 68°F to 77°F (20°C to 25°C).

Keep GLUMETZA and all medicines out of the reach of children.

General information about the safe and effective use of GLUMETZA

Medicines are sometimes prescribed for purposes other than those listed in a Patient Information leaflet. Do not use GLUMETZA for a condition for which it was not prescribed. Do not give GLUMETZA to other people, even if they have the same symptoms you have. It may harm them.

You can ask your pharmacist or doctor for information about GLUMETZA that is written for health professionals.

What are the ingredients in GLUMETZA?

Active Ingredient: metformin hydrochloride

Inactive Ingredient: 500 mg tablet: coloring, hypromellose, magnesium stearate, microcrystalline cellulose and polyethylene oxide.

1,000 mg tablet: colloidal silicon dioxide, polyvinyl alcohol, crospovidone, glyceryl dibehenate, polyacrylate dispersion, hypromellose, talc, polyethylene glycol, titanium dioxide, simethicone emulsion, polysorbate and coloring.

Distributed by: Salix Pharmaceuticals, a division of Bausch Health US, LLC, Bridgewater, NJ 08807 USA

Patented. See https://patents.salix.com for US patent information.

Glumetza is a trademark of Salix Pharmaceuticals, Inc. or its affiliates.

© 2024 Salix Pharmaceuticals, Inc. or its affiliates

For more information, go to www.GlumetzaXR.com or call 1-800-321-4576.

This Patient Information has been approved by the U.S. Food and Drug Administration.

Revised: 02/2024

9618905 20005381

Package/Label Display Panel – 500 mg

NDC 68012-004-50
Rx only

Glumetza®
(metformin hydrochloride
extended-release tablets)

500 mg

ONCE DAILY

100 Tablets

Salix

Package/Label Display Panel – 500 mg

NDC 68012-002-13
Rx only

Glumetza®
(metformin hydrochloride
extended-release tablets)

500 mg

ONCE DAILY

100 Tablets

Salix

Package/Label Display Panel – 1,000 mg

NDC 68012-003-16
Rx only

Glumetza®

(metformin hydrochloride
extended-release tablets)

1,000 mg

ONCE DAILY

90 Tablets
Salix